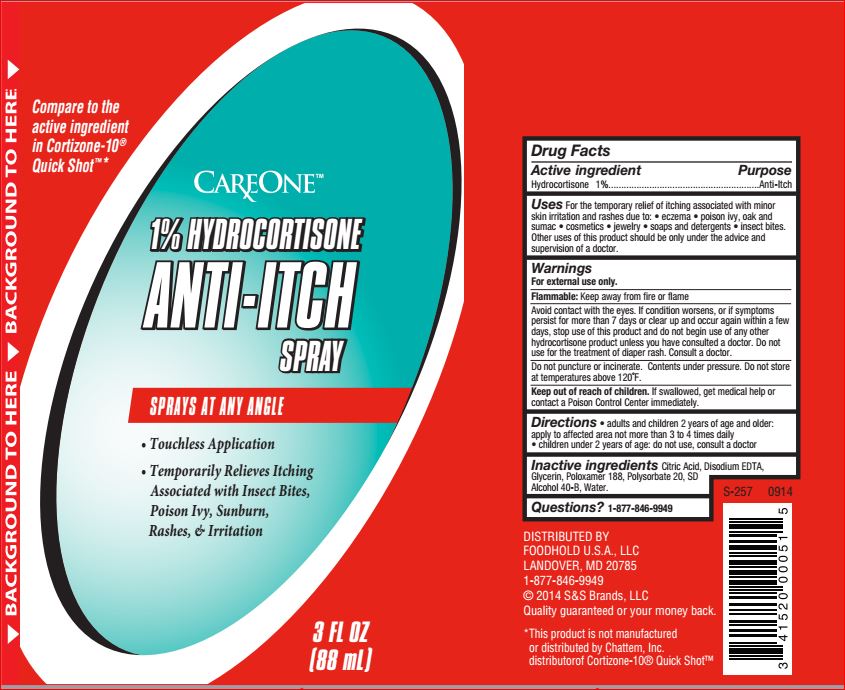 DRUG LABEL: Anti-Itch
NDC: 41520-366 | Form: SPRAY
Manufacturer: Car One
Category: otc | Type: HUMAN OTC DRUG LABEL
Date: 20180619

ACTIVE INGREDIENTS: Hydrocortisone 1 g/100 g
INACTIVE INGREDIENTS: CITRIC ACID MONOHYDRATE; EDETATE DISODIUM; Glycerin; Poloxamer 188; Polysorbate 20; ALCOHOL; Water

Car One LabsDrug Facts

Active ingredient Purpose

Hydrocortisone - 1.00% Anti-itch

Uses

For the temporary relief of itching associated with minor
skin irritation and rashes due to: • eczema • poison ivy, oak and
sumac • cosmetics • jewelry • soaps and detergents • insect
bites. Other uses of this product should be only under the advice
and supervision of a doctor.

Warnings
For external use only.
Flammable: Keep away from fire or flame
Avoid contact with the eyes. If condition worsens, or if symptoms
persist for more than 7 days or clear up and occur again within a
few days, stop use of this product and do not begin use of any
other hydrocortisone product unless you have consulted a doctor.
Do not use for the treatment of diaper rash. Consult a doctor.
Do not puncture or incinerate. Contents under pressure. Do not
store at temperatures above 120˚F

Keep out of reach of the children

If swallowed, get medical help or contact a Poison Control Center right away

Directions

• adults and children 2 years of age and older:
apply to affected area not more than 3 to 4 times daily
• children under 2 years of age: do not use, consult a doctor

Inactive ingredients

Citric Acid, Disodium EDTA, Glycerin, Poloxamer 188, Polysorbate 20, SD Alcohol 40-B, Water